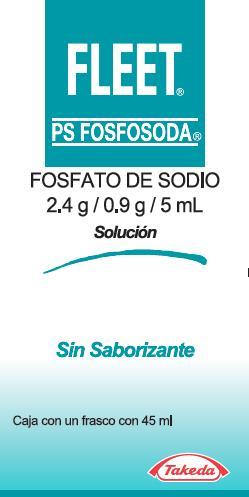 DRUG LABEL: Fleet
NDC: 0132-0539 | Form: LIQUID
Manufacturer: C.B. Fleet Company, Inc.
Category: otc | Type: HUMAN OTC DRUG LABEL
Date: 20160129

ACTIVE INGREDIENTS: SODIUM PHOSPHATE, DIBASIC, HEPTAHYDRATE 2.7 g/45 mL; SODIUM PHOSPHATE, MONOBASIC 7.2 g/45 mL
INACTIVE INGREDIENTS: WATER; GLYCERIN; SACCHARIN SODIUM; SODIUM BENZOATE

Active Ingredient (in each Tablespoon)

Monobasic Sodium Phosphate 7.2 g.................Saline Laxative / Bowel Cleanser

Dibasic Sodium Phosphate 2.7 g......................Saline Laxative / Bowel Cleanser

Uses

- relief of occasional constipation
- to help clean out the bowel before medical procedures

WARNINGS AND PRECAUTIONS

Taking more than the recommended dose in 24 hours can be harmful.

Do not use

- if you have congestive heart failure
- if you have serious kidney problemsin children under 5 years of age

Ask a doctor before use if you are

- under a doctor's care for any medical condition
- on a low salt diet

Ask a doctor or pharmacist before use if you are taking any other prescription or non-prescription drugs.

Ask a doctor before using any laxative if you have

- abdominal (belly) pain, nausea, or vomitting
- a change in your daily bowel movements that lasts more than 2 weeks
- already used another laxative daily for constipation for more than 1 week

Stop use and ask a doctor if you

- have any rectal bleeding
- do not have a bowel movement within 6 hours of taking this product
- have any symptoms that your body is losing more fluids than you are drinking. This is called dehydration. Early symptoms of dehydration include - feeling thristy - dizziness - urinating less often than normal - vomiting

These symptoms may be signs of serious problems.

Keep out of reach of children

In case of overdose, get medical help or contact a Poison Control Center right away.

Directions

Laxative Dose and Directions
Ages (years) | Step 1 | Step 2 | 24 Hour Max Dose*
12 years & older | Mix 1 tablespoon in a full glass of cold liquid (8 fl oz). Drink | Drink at least 1 extra full glass of liquid (8 fl oz). | 3 tablespoons
10 to 11 years | Mix 1 tablespoon in a full glass of cold liquid (8 fl oz). Drink | Drink at least 1 extra full glass of liquid (8 fl oz). | 1 tablespoon
5 to 9 years | Mix 1/2 tablespoon in a full glass of cold liquid (8 fl oz). Drink | Drink at least 1 extra full glass of liquid (8 fl oz). | 1/2 tablespoon
Under 5 years | Do Not Use | Do Not Use | Do Not Use

* Take no more than this amount in a 24 hour period.

Use as a laxative for relief of occasional constipation.

- follow the dose and directions.
- do not take more unless directed by a doctor. See Warnings.
- drink as much extra liquids as you can to help replace the fluids you are losing during bowel movements.

Other Information

- 1 tablespoon contains: sodium 1668 mg
- this product is sugar-free
- this product usually causes a person to have a bowel movement in 30 minutes to 6 hours
- chill this product in refrigerator to improve the taste. Do not freeze

Inactive Ingredients

glycerin, purified water, saccharin sodium, sodium benzoate

Questions?

1-888-999-9711